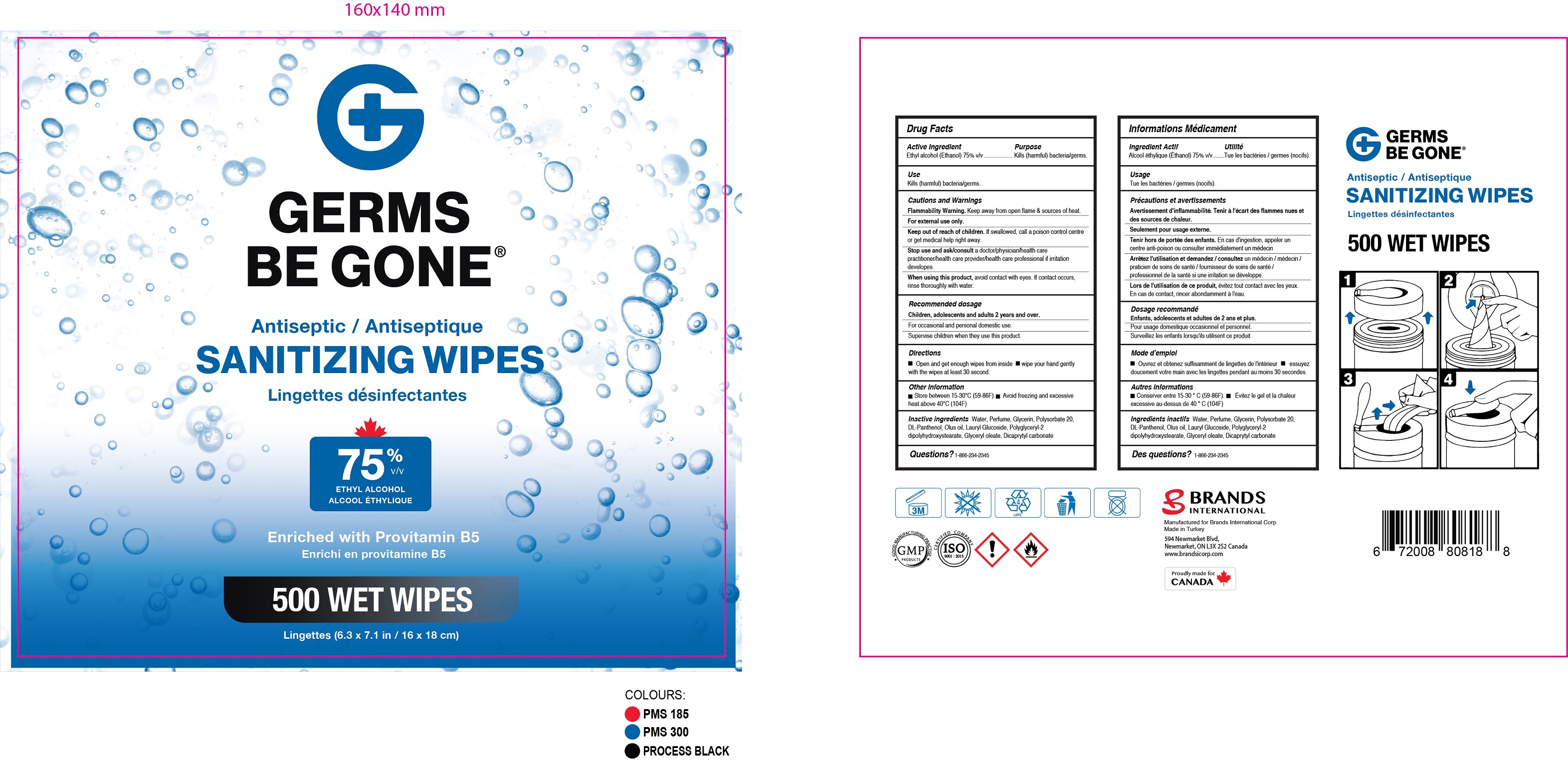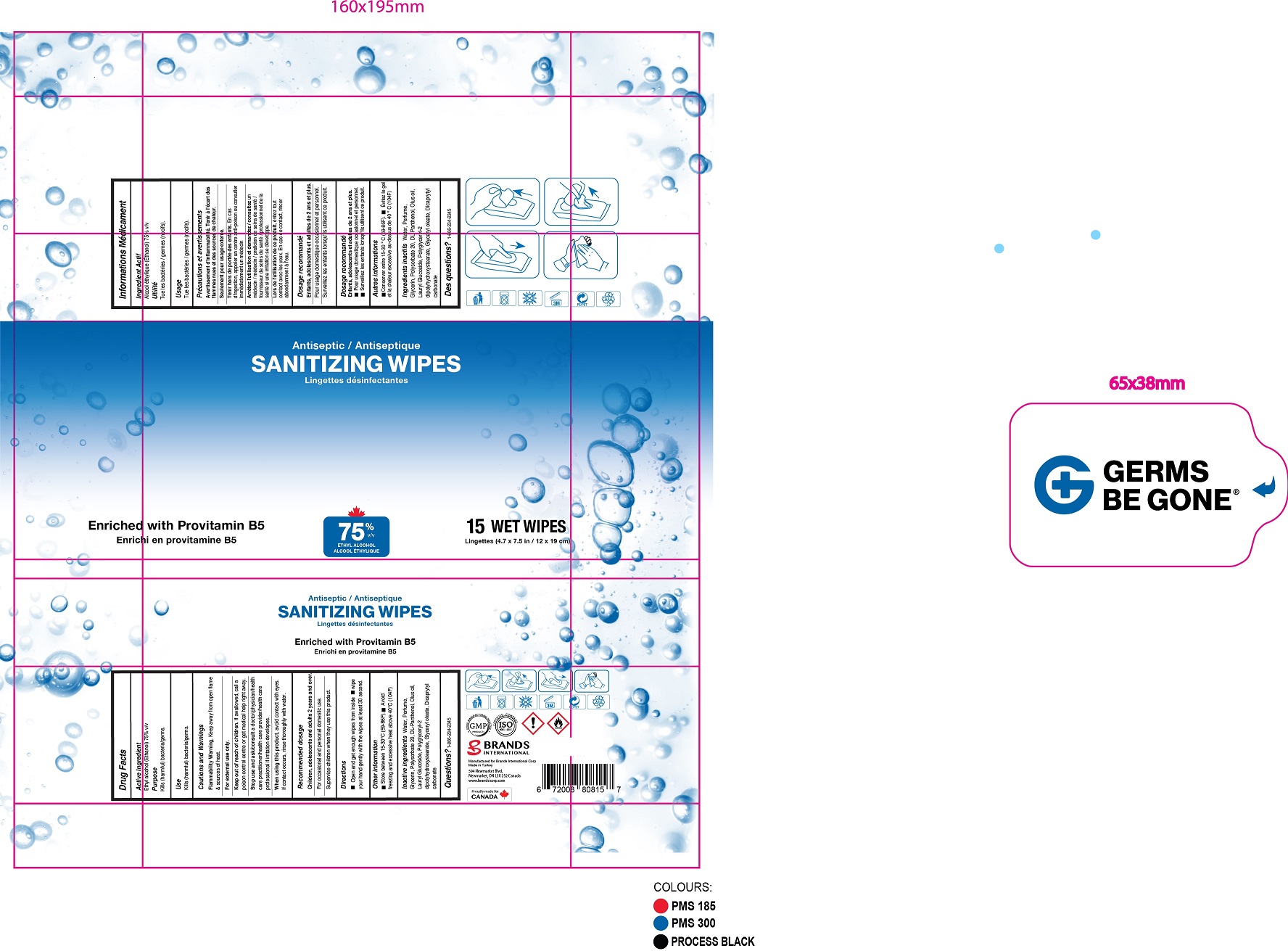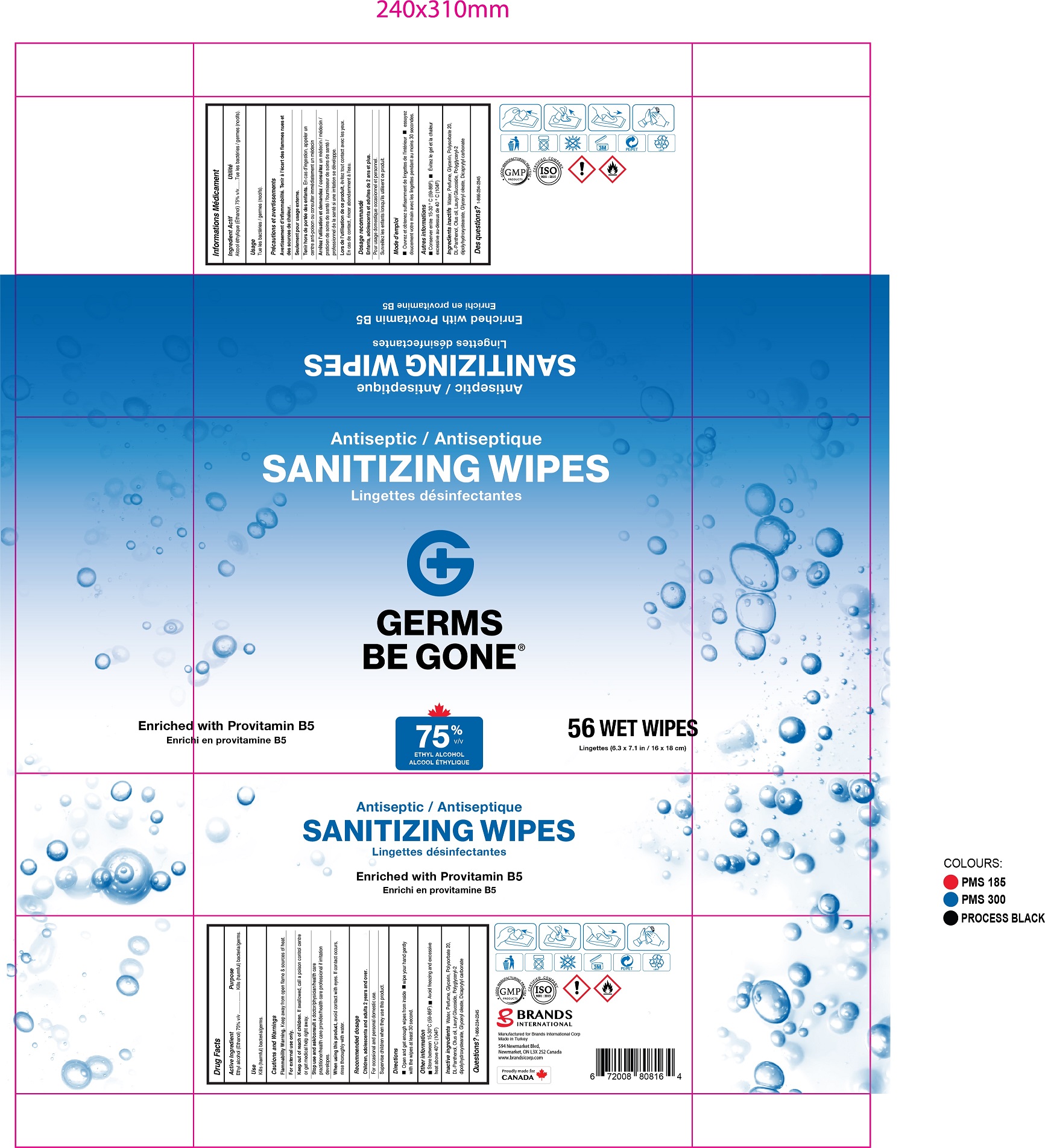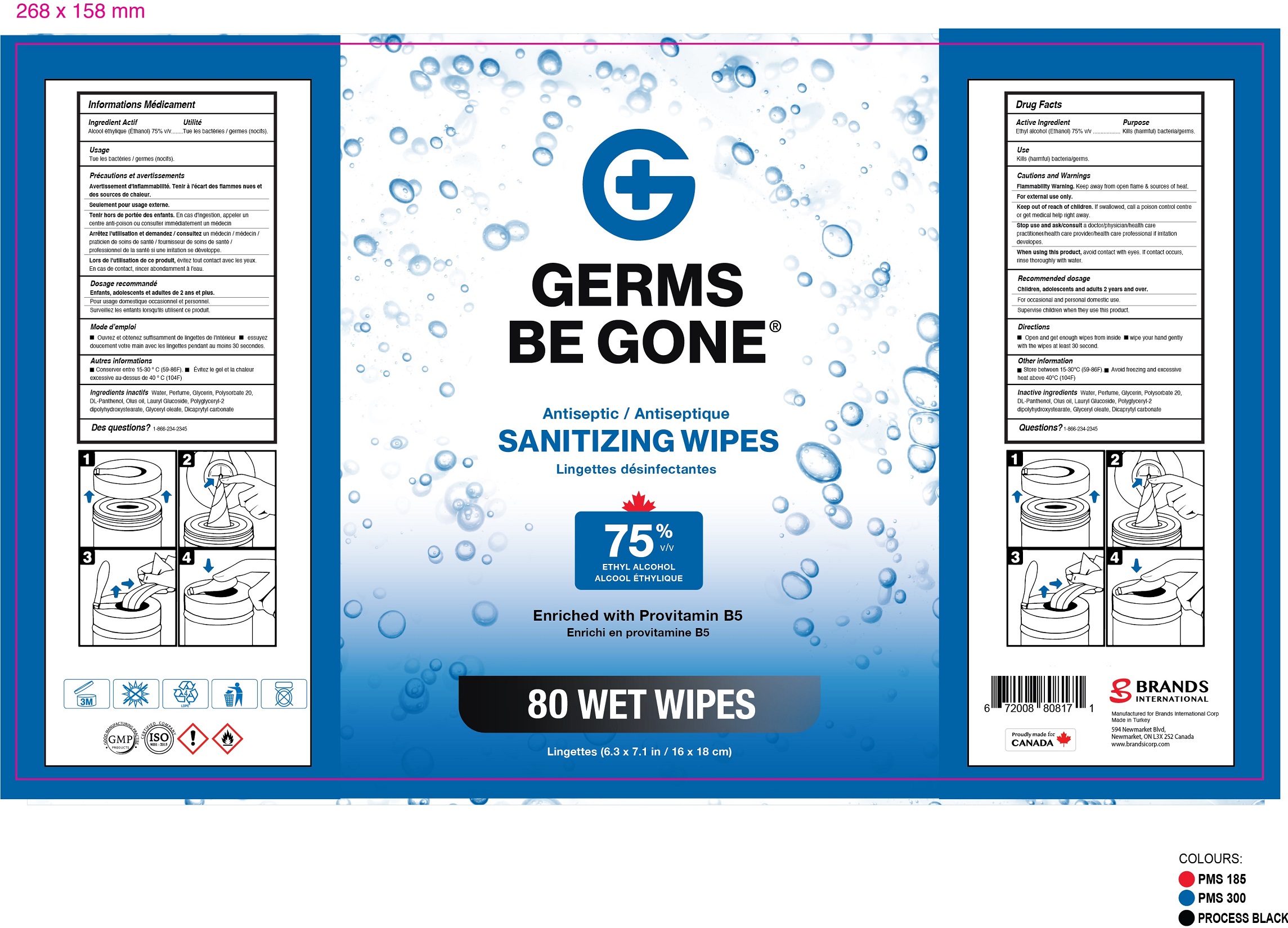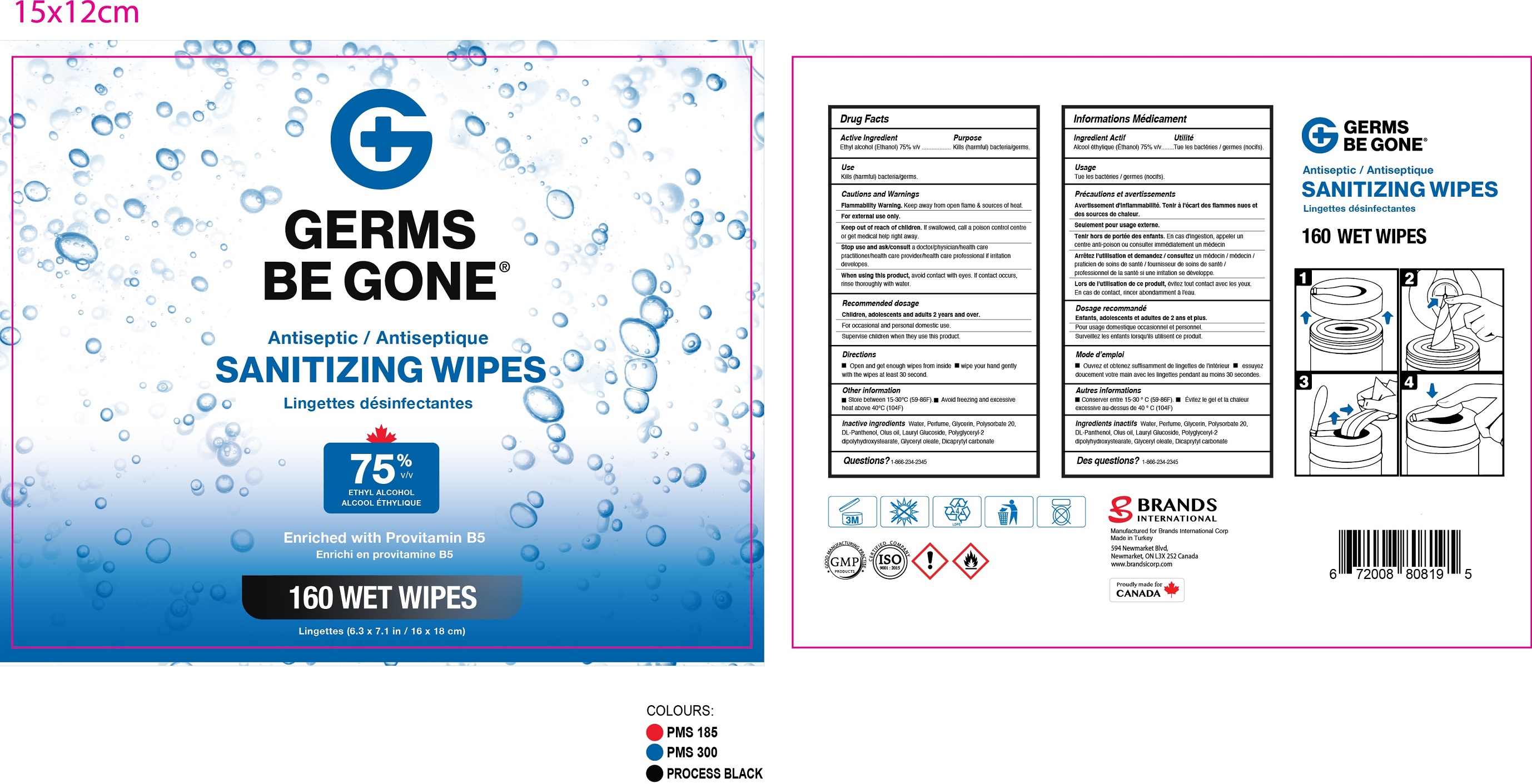 DRUG LABEL: Germs Be Gone Antiseptic wipes
NDC: 50157-530 | Form: CLOTH
Manufacturer: Brands International corporation
Category: otc | Type: HUMAN OTC DRUG LABEL
Date: 20220826

ACTIVE INGREDIENTS: ALCOHOL 75 g/100 mL
INACTIVE INGREDIENTS: POLYSORBATE 20; GLYCERIN; PANTHENOL; WATER; LAURYL GLUCOSIDE; POLYGLYCERYL-2 DIPOLYHYDROXYSTEARATE; GLYCERYL OLEATE; DICAPRYLYL CARBONATE

Germs Be Gone Antiseptic wipes.

Active Ingredient(s)

Ethyl Alcohol 75%

Purpose

Kills (harmful) bacteria/germs.

Use

Kills (harmful) bacteria/germs.

Warnings

Flammabillty Warning : Keep away from open flame & sources of heat.

For extenal use only.

WHEN USING

Avoid contact with eyes. if contact occurs, rinse thoroughly with water.

STOP USE

A doctor/physician care practitoner/health care provider care professional if irritation develops.

Keep out of reach of children. If swallowed, get medical help or contact a Poison Control Center right away.

Directions

- Open and get enough wipes from inside
- wipe your hand genlty with the wipes at least 30 second.

Other information

- store between 15-30C (59-86F)
- Avoid freezing and excessive heat above 40C (104F)

Inactive ingredients

Water, Glycerin,Parfume,Dicaprylyl Carbonate,Glyceryl Oleate,Lauryl glucoside,Olus oil,Polyglyceryl-2Dipolyhydroxystearate

Panthenol,Polysorbate 20.